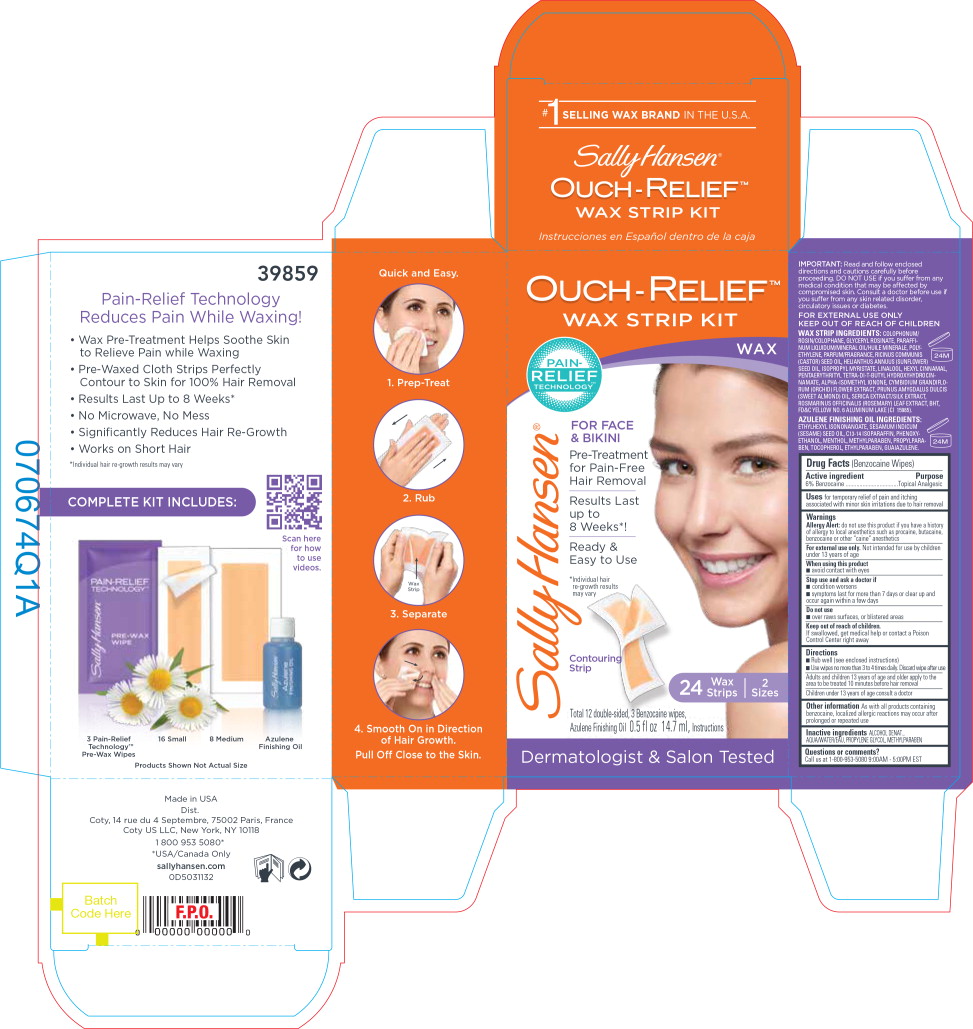 DRUG LABEL: Sally Hansen Ouch-Relief Wax Strip Kit
NDC: 66184-162 | Form: KIT | Route: TOPICAL
Manufacturer: Coty US LLC
Category: otc | Type: HUMAN OTC DRUG LABEL
Date: 20211019

ACTIVE INGREDIENTS: BENZOCAINE 6 g/1 1
INACTIVE INGREDIENTS: WATER; PROPYLENE GLYCOL; METHYLPARABEN

Drug Facts

(Benzocaine Wipes)

Active ingredient

6% Benzocaine

Purpose

Topical Analgesic

Uses

for temporary relief of pain and itching associated with minor skin irritations due to hair removal

Warnings

Allergy Alert: do not use this product if you have a history of allergy to local anesthetics such as procaine, butacaine, benzocaine or other “caine” anesthetics

For external use only. Not intended for use by children under 13 years of age

When using this product

- avoid contact with eyes

Stop use and ask a doctor if

- condition worsens
- symptoms last for more than 7 days or clear up and occur again within a few days

Do not use

- over raws surfaces, or blistered areas

Keep out of reach of children.

If swallowed, get medical help or contact a Poison Control Center right away

Directions

Rub well (see enclosed instructions)

Use wipes no more than 3 to 4 times daily. Discard wipe after use

Adults and children 13 years of age and older apply to the area to be treated 10 minutes before hair removal

Children under 13 years of age consult a doctor

Other information

As with all products containing benzocaine, localized allergic reactions may occur after prolonged or repeated use

Inactive ingredients

ALCOHOL DENAT., AQUA/WATER/EAU, PROPYLENE GLYCOL, METHYLPARABEN

Questions or comments?

Call us at 1-800-953-5080 9:00AM - 5:00PM EST

Principal Display Panel - Sally Hansen Ouch-Relief Wax Strip Kit Label

OUCH-RELIEF™
WAX STRIP KIT

WAX

PAIN-
RELIEF
TECHNOLOGY™

Sally Hansen®

FOR FACE
& BIKINI

Pre-Treatment
for Pain-Free
Hair Removal

Results Last
Up to
8 Weeks!*

Ready &
Easy to Use

*Individual hair
re-growth results
may vary

Contouring
Strip

24 Wax
Strips

2
Sizes

Total 12 double sided, 3 Benzocaine wipes,
Azulene Finishing Oil 0.5 fl oz 14.7 ml, Instructions

Dermatologist & Salon Tested